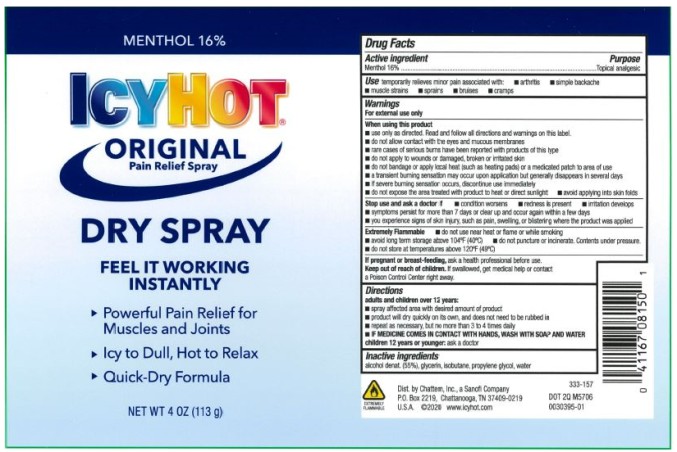 DRUG LABEL: Icy Hot Dry
NDC: 41167-0815 | Form: SPRAY
Manufacturer: Chattem, Inc.
Category: otc | Type: HUMAN OTC DRUG LABEL
Date: 20260114

ACTIVE INGREDIENTS: MENTHOL 16 g/100 g
INACTIVE INGREDIENTS: ALCOHOL; GLYCERIN; ISOBUTANE; PROPYLENE GLYCOL; WATER

Icy Hot Dry Spray

ICY HOT DRY SPRAY

Drug Facts

Active ingredient

Menthol 16%

Purpose

Topical analgesic

Use

temporarily relieves minor pain associated with: ■ arthritis ■ simple backache ■ muscle strains

■ sprains ■ bruises ■ cramps

Warnings

For external use only

When using this product

■ use only as directed. Read and follow all directions and warnings on this label.

■ do not allow contact with the eyes and mucous membranes

■ rare cases of serious burns have been reported with products of this type

■ do not apply to wounds or damaged, broken or irritated skin

■ do not bandage or apply local heat (such as heating pads) or a medicated patch to area of use

■ a transient burning sensation may occur upon application but generally disappears in several days

■ if severe burning sensation occurs, discontinue use immediately

■ do not expose the area treated with product to heat or direct sunlight

■ avoid applying into skin folds

Stop use and ask a doctor if

■ condition worsens

■ redness is present

■ irritation develops

■ symptoms persist for more than 7 days or clear up and occur again within a few days

■ you experience signs of skin injury, such as pain, swelling, or blistering where the product was applied

Extremely Flammable

■ do not use near heat or flame or while smoking

■ avoid long term storage above 104°F (40°C)

■ do not puncture or incinerate. Contents under pressure.

■ do not store at temperatures above 120°F (49°C)

If pregnant or breast-feeding,

ask a health professional before use.

Keep out of reach of children.

If swallowed, get medical help or contact a Poison Control Center right away.

Directions

adults and children over 12 years:

■ spray affected area with desired amount of product

■ product will dry quickly on its own, and does not need to be rubbed in

■ repeat as necessary, but no more than 3 to 4 times daily

■ IF MEDICINE COMES IN CONTACT WITH HANDS, WASH WITH SOAP AND WATER

children 12 years or younger: ask a doctor

Inactive ingredients:

alcohol denat. (55%), glycerin, isobutane, propylene glycol, water

PRINCIPAL DISPLAY PANEL

ICYHOT
ORIGINAL
Pain Relief Spray
DRY SPRAY
FEEL IT WORKING
INSTANTLY
NET WT 4 OZ (113g)